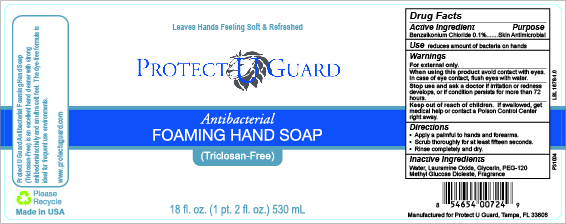 DRUG LABEL: Protect U Guard Antibacterial Foaming
NDC: 71788-001 | Form: LIQUID
Manufacturer: Protect U Guard, LLC
Category: otc | Type: HUMAN OTC DRUG LABEL
Date: 20200604

ACTIVE INGREDIENTS: BENZALKONIUM CHLORIDE 0.1 g/100 mL
INACTIVE INGREDIENTS: LAURAMINE OXIDE; PEG-120 METHYL GLUCOSE DIOLEATE; WATER; GLYCERIN

Active Ingredient

Benzalkonium Chloride 0.1%

Purpose

Skin Antimicrobial

Use

Reduces amount of bacteria on hands

Warnings

For external use only.

When using this product avoid contact with eyes. In case of eye contact, flush eyes with water.

Stop Use and Ask a Doctor of irritation or redness develops, or if condition persists for more than 72 hours.

Keep out of reach of children. If swallowed, get medical help or contact a Poison Control Center right away.

When using this product avoid contact with eyes. In case of eye contact, flush eyes with water.

Stop use and ask a doctor if irritation or redness develops, or if condition persists for more than 72 hours.

Keep out of reach of children. If swallowed, get medical help or contact a Poison Control Center right away.

Directions

Apply a palmful to hands and forearms.

Scrub thoroughly for at least fifteen seconds

Rinse completely and dry.

Inactive Ingredients

Water, Lauramine Oxide, Glycerin, PEG-120 Methyl Glucose Dioleate, Fragrance